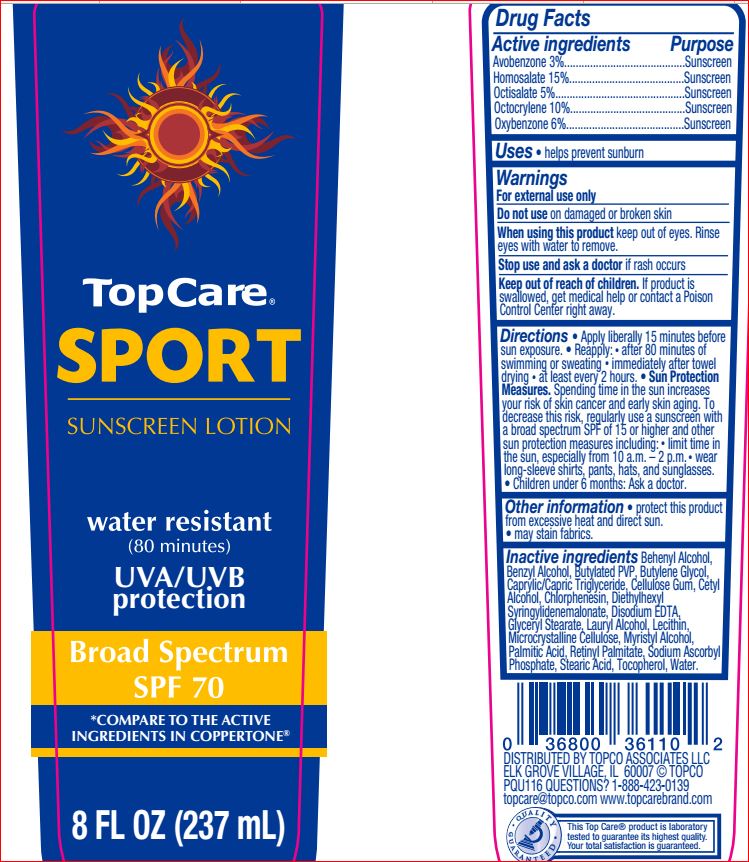 DRUG LABEL: Sunscreen SPF 70
NDC: 36800-716 | Form: LOTION
Manufacturer: Top Care
Category: otc | Type: HUMAN OTC DRUG LABEL
Date: 20180703

ACTIVE INGREDIENTS: AVOBENZONE 3 g/100 mL; HOMOSALATE 15 g/100 mL; OCTISALATE 5 g/100 mL; OCTOCRYLENE 10 1/100 mL; OXYBENZONE 6 g/100 mL
INACTIVE INGREDIENTS: DOCOSANOL; BENZYL ALCOHOL; BUTYLENE GLYCOL; MEDIUM-CHAIN TRIGLYCERIDES; CARBOXYMETHYLCELLULOSE SODIUM; CETYL ALCOHOL; CHLORPHENESIN; DIETHYLHEXYL SYRINGYLIDENEMALONATE; EDETATE DISODIUM; GLYCERYL MONOSTEARATE; LAURYL ALCOHOL; LECITHIN, SOYBEAN; CELLULOSE, MICROCRYSTALLINE; MYRISTYL ALCOHOL; PALMITIC ACID; VITAMIN A PALMITATE; SODIUM ASCORBYL PHOSPHATE; STEARIC ACID; TOCOPHEROL; WATER

Daylogic
Drug Facts

Active ingredients

Avobenzone 3%

Homosalate 15%

Octisalate 5%

Octocrylene 10%

Oxybenzone 6%

Purpose

Sunscreen

Uses

Uses • helps prevent sunburn

Warnings

For external use only

Do not use

on damaged or broken skin

When using this product

keep out of eyes. Rinse with water to remove.

Stop use and ask a doctor

if rash occurs.

Keep out of reach of children.

If product is swallowed, get medical help or contact a Poison Control Center right away.

Directions

- apply liberally 15 minutes before sun exposure
- reapply:
- after 80 minutes of swimming or sweating
- immediately after towel drying
- at least 2 hours
- Sun Protection Measures. Spending time in the sun increases your risk of skin cancer and early skin aging. To decrease this risk, regularly use a sunscreen with a broad spectrum SPF of 15 or higher and other sun protection measures including:
- limit time in the sun, especially from 10 a.m. -2 p.m.
- wear long-sleeve shirts, pants, hats, and sunglasses
- children under 6 months: Ask a doctor

Inactive ingredients

Behenyl Alcohol, Benzyl Alcohol, Butylated PVP, Butylene Glycol, Caprylic/Capric Triglyceride, Cellulose Gum, Cetyl Alcohol, Chlorphenesin, Diethylhexyl Syringylidenemalonate, Disodium EDTA, Glyceryl Stearate, Lauryl Alcohol, Lecithin, Microcrystalline Cellulose, Myristyl Alcohol, Palmitic Acid, Retinyl Palmitate, Sodium Ascorbyl Phosphate, Stearic Acid, Tocopherol, Water.

Other information

- protect this product from excessive heat and direct sun
- may stain fabrics.